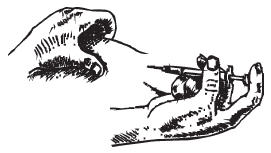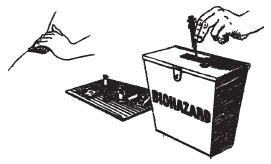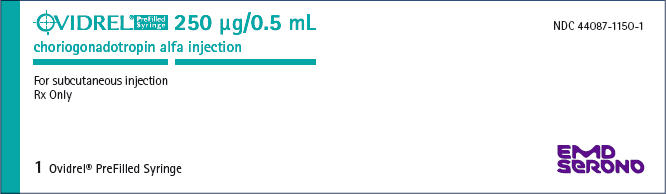 DRUG LABEL: Ovidrel
NDC: 44087-1150 | Form: INJECTION, SOLUTION
Manufacturer: EMD Serono, Inc.
Category: prescription | Type: HUMAN PRESCRIPTION DRUG LABEL
Date: 20231226

ACTIVE INGREDIENTS: CHORIOGONADOTROPIN ALFA 250 ug/0.5 mL
INACTIVE INGREDIENTS: MANNITOL; PHOSPHORIC ACID; METHIONINE; POLOXAMER 188; SODIUM HYDROXIDE; WATER

OVIDREL® PreFilled Syringe
(choriogonadotropin alfa injection)

FOR SUBCUTANEOUS USE

DESCRIPTION

Ovidrel® PreFilled Syringe (choriogonadotropin alfa injection) is a sterile liquid preparation of choriogonadotropin alfa (recombinant human Chorionic Gonadotropin, r-hCG). Choriogonadotropin alfa is a water soluble glycoprotein consisting of two non-covalently linked subunits - designated α and β - consisting of 92 and 145 amino acid residues, respectively, with carbohydrate moieties linked to ASN-52 and ASN-78 (on alpha subunit) and ASN-13, ASN-30, SER-121, SER-127, SER-132 and SER-138 (on beta subunit). The primary structure of the α - chain of r-hCG is identical to that of the α - chain of hCG, FSH and LH. The glycoform pattern of the α - subunit of r-hCG is closely comparable to urinary derived hCG (u-hCG), the differences mainly being due to the branching and sialylation extent of the oligosaccharides. The β - chain has both O- and N-glycosylation sites and its structure and glycosylation pattern are also very similar to that of u-hCG.

The production process involves expansion of genetically modified Chinese Hamster Ovary (CHO) cells from an extensively characterized cell bank into large scale cell culture processing. Choriogonadotropin alfa is secreted by the CHO cells directly into the cell culture medium that is then purified using a series of chromatographic steps. This process yields a product with a high level of purity and consistent product characteristics including glycoforms and biological activity. The biological activity of choriogonadotropin alfa is determined using the seminal vesicle weight gain test in male rats described in the "Chorionic Gonadotrophins" monograph of the European Pharmacopoeia. The in vivo biological activity of choriogonadotropin alfa has been calibrated against the third international reference preparation IS75/587 for chorionic gonadotropin.

Ovidrel® PreFilled Syringe is a sterile, liquid intended for subcutaneous (SC) injection. Each Ovidrel® PreFilled Syringe is filled with 0.515 mL containing 257.5 µg of choriogonadotropin alfa, 28.1 mg mannitol, 505 µg 85% O-phosphoric acid, 103 µg L-methionine, 51.5 µg Poloxamer 188, Sodium Hydroxide (for pH adjustment), and Water for Injection to deliver 250 µg of choriogonadotropin alfa in 0.5 mL. The pH of the solution is 6.5 to 7.5.

Therapeutic Class: Infertility

CLINICAL PHARMACOLOGY

The physicochemical, immunological, and biological activities of recombinant hCG are comparable to those of placental and human pregnancy urine-derived hCG. Choriogonadotropin alfa stimulates late follicular maturation and resumption of oocyte meiosis, and initiates rupture of the pre-ovulatory ovarian follicle. Choriogonadotropin alfa, the active component of Ovidrel® PreFilled Syringe , is an analogue of Luteinizing Hormone (LH) and binds to the LH/hCG receptor of the granulosa and theca cells of the ovary to effect these changes in the absence of an endogenous LH surge. In pregnancy, hCG, secreted by the placenta, maintains the viability of the corpus luteum to provide the continued secretion of estrogen and progesterone necessary to support the first trimester of pregnancy. Ovidrel® PreFilled Syringe is administered when monitoring of the patient indicates that sufficient follicular development has occurred in response to FSH treatment for ovulation induction.

Pharmacokinetics

When given by intravenous administration, the pharmacokinetic profile of Ovidrel® followed a biexponential model and was linear over a range of 25 µg to 1000 µg. Pharmacokinetic parameter estimates following SC administration of Ovidrel® 250 µg to females are presented in Table 1.

Table 1: Pharmacokinetic Parameters (mean ± SD) of r-hCG after Single-Dose Administration of Ovidrel® in Healthy Female Volunteers
 | Ovidrel® 250 µg SC
Cmax (IU/L) | 121 ± 44
tmax (h) [median (range)] | 24 (12-24)
AUC (h∙IU/L) | 7701 ± 2101
t½ (h) | 29 ± 6
F | 0.4 ± 0.1
Cmax: peak concentration (above baseline), tmax: time of Cmax, AUC: total area under the curve, t½: elimination half-life, F: bioavailability

Absorption

Following subcutaneous administration of Ovidrel® 250 µg, maximum serum concentration (121 ± 44 IU/L) is reached after approximately 12 to 24 hours. The mean absolute bioavailability of Ovidrel® following a single subcutaneous injection to healthy female volunteers is about 40%.

Distribution

Following intravenous administration of Ovidrel® 250 µg to healthy down-regulated female volunteers, the serum profile of hCG is described by a two-compartment model with an initial half-life of 4.5 ± 0.5 hours. The volume of the central compartment is 3.0 ± 0.5 L and the steady state volume of distribution is 5.9 ± 1.0 L.

Metabolism/Excretion

Following subcutaneous administration of Ovidrel®, hCG is eliminated from the body with a mean terminal half-life of about 29 ± 6 hours. After intravenous administration of Ovidrel® 250 µg to healthy down-regulated females, the mean terminal half-life is 26.5 ± 2.5 hours and the total body clearance is 0.29 ± 0.04 L/h. One-tenth of the dose is excreted in the urine.

Pharmacodynamics

In female subjects on oral contraception after an initial latency period, Ovidrel® induced a clear increase in androstenedione serum levels by 24 hours after dosing. Pharmacodynamic studies in females determined that the relationship of Ovidrel® pharmacokinetics to pharmacologic effect of Ovidrel® are complex and vary with the pharmacodynamic marker examined. In general pharmacologic effects are not proportional to exposure and in some cases appear to be near maximal at a 250 µg dose.

Population pharmacokinetics and pharmacodynamics

In patients undergoing in-vitro fertilization/embryo transfer given Ovidrel® subcutaneously to trigger ovulation, the results of a population PK/PD analysis generally supported the data obtained in healthy subjects. Pharmacokinetic parameters for Ovidrel® include a median elimination half-life of 29.2 hours, median apparent clearance (Cl/F) of 0.51 L/hr and median apparent volume of distribution (V/F) of 21.4 L.

Bioequivalence of Formulations

Ovidrel® PreFilled Syringe (choriogonadotropin alfa injection) has been determined to be bioequivalent to Ovidrel® (choriogonadotropin alfa for injection) based on the statistical evaluation of AUC and Cmax. A summary of the Ovidrel® PreFilled Syringe pharmacokinetic parameters is presented in Table 2.

Table 2: Summary of Ovidrel® PreFilled Syringe Pharmacokinetic Parameters
Parameter | Cmax (mIU/mL) | AUClast (mIU∙h/mL) | AUC (mIU∙h/mL) | AUCextrapolated (%) | tmax (h)
Mean | 125 | 10050 | 10350 | 2.85 | 20.0
(Min-Max) | (68.0-294) | (5646-14850) | (5800-15100) | (1.08-6.27) | (9.00-48.0)
Abbreviations are: Cmax: peak concentration (above baseline); tmax : time of Cmax

Special populations

Safety, efficacy, and pharmacokinetics of Ovidrel® PreFilled Syringe in patients with renal or hepatic insufficiency have not been established.

Drug-Drug Interactions

No drug-drug interaction studies have been conducted. Administration of Ovidrel® PreFilled Syringe may interfere with the interpretation of pregnancy tests. (see PRECAUTIONS.)

CLINICAL STUDIES

The safety and efficacy of Ovidrel® have been examined in three well-controlled studies in women; two studies for assisted reproductive technologies (ART) and one study for ovulation induction (OI).

Assisted Reproductive Technologies (ART)

The safety and efficacy of Ovidrel® 250 µg and Ovidrel® 500 µg administered subcutaneously versus 10,000 USP Units of an approved urinary-derived hCG product administered intramuscularly were assessed in a randomized, open-label, multicenter study in infertile women undergoing in vitro fertilization and embryo transfer (Study 7927). The study was conducted in 20 U.S. centers.

The primary efficacy parameter in this single-cycle study was the number of oocytes retrieved. 297 patients entered the study, of whom 94 were randomized to receive Ovidrel® 250 µg. The number of oocytes retrieved was similar for the Ovidrel® and urinary-derived hCG (10,000 USP Units) treatment groups. The efficacy of Ovidrel® 250 µg and Ovidrel® 500 µg were both found to be clinically and statistically equivalent to that of the approved urinary-derived hCG product and to each other. The efficacy results for the patients who received Ovidrel® 250 µg are summarized in Table 3.

Table 3: Efficacy Outcomes of r-hCG in ART (Study 7927)
Parameter | Ovidrel® 250 µg (n = 94)
Mean number of oocytes retrieved per patient | 13.60
Mean number of mature oocytes retrieved per patient | 7.6
Mean number of 2 PN fertilized oocytes per patient | 7.2
Mean number of 2 PN or cleaved embryos per patient | 7.6
Implantation rate per embryo transferred (%) | 18.7
Mean mid-luteal serum progesterone levels (nmol/L [nmol/L ÷ 3.18 = ng/mL]) | 423
Clinical pregnancy rate per initiated treatment cycle (%) [Clinical pregnancy was defined as a pregnancy during which a fetal sac (with or without heartbeat activity) was detected by ultrasound on day 35-42 after hCG administration)] | 35.1
Clinical pregnancy rate per transfer (%) | 36.3

For the 33 patients who achieved a clinical pregnancy with Ovidrel® 250 µg, the outcomes of the pregnancies are presented in Table 4.

Table 4: Pregnancy Outcomes of r-hCG in ART (Study 7927)
Parameter | Ovidrel® 250 µg (n = 33)
Clinical pregnancies not reaching term | 4 (12.1%)
Live births | 29 (87.9%)
Singleton | 20 (69.0%)
Multiple birth | 9 (31.0%)

The safety and efficacy of Ovidrel® 250 µg administered subcutaneously versus 5,000 IU of an approved urinary-derived hCG product administered subcutaneously were assessed in a second, randomized, multicenter study in infertile women undergoing in vitro fertilization and embryo transfer (Study 7648). This double-blinded study was conducted in nine centers in Europe and Israel.

The primary efficacy parameter in this single-cycle study was the number of oocytes retrieved per patient. 205 patients entered the study, of whom 97 received Ovidrel® 250 µg. The efficacy of Ovidrel® 250 µg was found to be clinically and statistically equivalent to that of the approved urinary-derived hCG product. The results for the 97 patients who received Ovidrel® 250 µg are summarized in Table 5.

Table 5: Efficacy Outcomes of r-hCG in ART (Study 7648)
Parameter | Ovidrel® 250 µg (n = 97)
Mean number of oocytes retrieved per patient | 10.6
Mean number of mature oocytes retrieved per patient | 10.1
Mean number of 2 PN fertilized oocytes per patient | 5.7
Mean number of 2 PN or cleaved embryos per patient | 5.1
Implantation rate per embryo transferred (%) | 17.4
Mean mid-luteal serum progesterone levels (nmol/L) [nmol/L ÷ 3.18 = ng/mL] | 394
Clinical pregnancy rate per initiated treatment cycle (%) [Clinical pregnancy was defined as a pregnancy during which a fetal sac (with or without heartbeat activity) was detected by ultrasound on day 35-42 after hCG administration)] | 33
Clinical pregnancy rate per transfer (%) | 37.6

For the 32 patients who achieved a clinical pregnancy with Ovidrel® 250 µg, the outcomes of the pregnancies are presented in Table 6.

Table 6: Pregnancy Outcomes of r-hCG in ART (Study 7648)
Parameter | Ovidrel® 250 µg (n = 32)
Clinical Pregnancies not reaching term | 6 (18.8%)
Live births | 26 (81.2%)
Singleton | 18 (69.2%)
Multiple birth | 8 (30.8%)

Ovulation Induction (OI)

The safety and efficacy of Ovidrel® 250 µg administered subcutaneously versus 5,000 IU of an approved urinary-derived hCG product administered intramuscularly were assessed in a double-blind, randomized, multicenter study in anovulatory infertile women (Study 8209) which was conducted in 19 centers in Australia, Canada, Europe and Israel.

The primary efficacy parameter in this single-cycle study was the patient ovulation rate. 242 patients entered the study, of whom 99 received Ovidrel® 250 µg. The efficacy of Ovidrel® 250 µg was found to be clinically and statistically equivalent to that of the approved urinary-derived hCG product. The results of those patients who received Ovidrel® 250 µg are summarized in Table 7.

Table 7: Efficacy Outcomes of r-hCG in OI (Study 8209)
Parameter | Ovidrel® 250 µg (n = 99)
Ovulation Rate | 91 (91.9%)
Clinical Pregnancy Rate [Clinical pregnancy was defined as a pregnancy during which a fetal sac (with or without heartbeat activity) was detected by ultrasound on day 35-42 after hCG administration.] | 22 (22%)

For the 22 patients who had a clinical pregnancy with Ovidrel® 250 µg, the outcome of the pregnancy is presented in Table 8.

Table 8: Pregnancy Outcomes of r-hCG in OI (Study 8209)
Parameter | Ovidrel® 250 µg (n = 22)
Clinical Pregnancies not reaching term | 7 (31.8%)
Live births | 15 (68.2%)
Singleton | 13 (86.7%)
Multiple birth | 2 (13.3%)

INDICATIONS AND USAGE

Ovidrel® PreFilled Syringe (choriogonadotropin alfa injection) is indicated for the induction of final follicular maturation and early luteinization in infertile women who have undergone pituitary desensitization and who have been appropriately pretreated with follicle stimulating hormones as part of an Assisted Reproductive Technology (ART) program such as in vitro fertilization and embryo transfer. Ovidrel® PreFilled Syringe is also indicated for the induction of ovulation (OI) and pregnancy in anovulatory infertile patients in whom the cause of infertility is functional and not due to primary ovarian failure.

Selection of Patients

1. Before treatment with gonadotropins is instituted, a thorough gynecologic and endocrinologic evaluation must be performed. This should include an assessment of pelvic anatomy. Patients with tubal obstruction should receive Ovidrel® PreFilled Syringe only if enrolled in an in vitro fertilization program.
2. Primary ovarian failure should be excluded by the determination of gonadotropin levels.
3. Appropriate evaluation should be performed to exclude pregnancy.
4. Patients in later reproductive life have a greater predisposition to endometrial carcinoma as well as a higher incidence of anovulatory disorders. A thorough diagnostic evaluation should always be performed in patients who demonstrate abnormal uterine bleeding or other signs of endometrial abnormalities before starting FSH and Ovidrel® PreFilled Syringe therapy.
5. Evaluation of the partner's fertility potential should be included in the initial evaluation.

CONTRAINDICATIONS

Ovidrel® PreFilled Syringe (choriogonadotropin alfa injection) is contraindicated in women who exhibit:

1. Prior hypersensitivity to hCG preparations or one of their excipients.
2. Primary ovarian failure.
3. Uncontrolled thyroid or adrenal dysfunction.
4. An uncontrolled organic intracranial lesion such as a pituitary tumor.
5. Abnormal uterine bleeding of undetermined origin (see "Selection of Patients").
6. Ovarian cyst or enlargement of undetermined origin (see "Selection of Patients").
7. Sex hormone dependent tumors of the reproductive tract and accessory organs.
8. Pregnancy.

WARNINGS

Gonadotropins, including Ovidrel® PreFilled Syringe (choriogonado-tropin alfa injection), should only be used by physicians who are thoroughly familiar with infertility problems and their management. Like other hCG products, Ovidrel® PreFilled Syringe is a potent gonadotropic substance capable of causing Ovarian Hyperstimulation Syndrome (OHSS) in women with or without pulmonary or vascular complications. The risks of gonadoptropin treatment should be considered for women with risk factors of thromboembolic events such as prior medical or family history. Gonadotropin therapy requires a certain time commitment by physicians and supportive health professionals, and requires the availability of appropriate monitoring facilities (see "Precautions/ Laboratory Tests"). Safe and effective induction of ovulation and use of Ovidrel® PreFilled Syringe in women requires monitoring of ovarian response with serum estradiol and transvaginal ultrasound on a regular basis.

Overstimulation of the Ovary Following hCG Therapy

Ovarian Enlargement

Mild to moderate uncomplicated ovarian enlargement which may be accompanied by abdominal distention and/or abdominal pain may occur in patients treated with FSH and hCG, and generally regresses without treatment within two or three weeks. Careful monitoring of ovarian response can further minimize the risk of overstimulation.

If the ovaries are abnormally enlarged on the last day of FSH therapy, choriogonadotropin alfa should not be administered in this course of therapy. This will reduce the risk of development of Ovarian Hyperstimulation Syndrome.

Ovarian Hyperstimulation Syndrome (OHSS)

OHSS is a medical event distinct from uncomplicated ovarian enlargement. Severe OHSS may progress rapidly (within 24 hours to several days) to become a serious medical event. It is characterized by an apparent dramatic increase in vascular permeability which can result in a rapid accumulation of fluid in the peritoneal cavity, thorax, and potentially, the pericardium. The early warning signs of development of OHSS are severe pelvic pain, nausea, vomiting, and weight gain. The following symptomatology has been seen with cases of OHSS: abdominal pain, abdominal distension, gastrointestinal symptoms including nausea, vomiting and diarrhea, severe ovarian enlargement, weight gain, dyspnea, and oliguria. Clinical evaluation may reveal hypovolemia, hemoconcentration, electrolyte imbalances, ascites, hemoperitoneum, pleural effusions, hydrothorax, acute pulmonary distress, and thromboembolic events (see "Pulmonary and Vascular Complications"). Transient liver function test abnormalities suggestive of hepatic dysfunction, which may be accompanied by morphologic changes on liver biopsy, have been reported in association with Ovarian Hyperstimulation Syndrome (OHSS).

OHSS occurred in 4 of 236 (1.7 %) patients treated with Ovidrel® 250 µg during clinical trials for ART and 3 of 99 (3.0%) patients treated in the OI trial. OHSS occurred in 8 of 89 (9.0%) patients who received Ovidrel® 500 µg. Two patients treated with Ovidrel® 500 µg developed severe OHSS.

OHSS may be more severe and more protracted if pregnancy occurs. OHSS develops rapidly; therefore, patients should be followed for at least two weeks after hCG administration. Most often, OHSS occurs after treatment has been discontinued and reaches its maximum at about seven to ten days following treatment. Usually, OHSS resolves spontaneously with the onset of menses. If there is evidence that OHSS may be developing prior to hCG administration (see "Precautions/Laboratory Tests"), the hCG must be withheld.

If severe OHSS occurs, treatment with gonadotropins must be stopped and the patient should be hospitalized.

A physician experienced in the management of this syndrome, or who is experienced in the management of fluid and electrolyte imbalances should be consulted.

Multiple Births

As with other hCG products, reports of multiple births have been associated with Ovidrel® treatment. In ART, the risk of multiple births correlates to the number of embryos transferred. Multiple births occurred in 17 of 55 live deliveries (30.9 %) experienced by women receiving Ovidrel® 250 µg in the ART studies. In the ovulation induction clinical trial, 2 of 15 live deliveries (13.3%) were associated with multiple births in women receiving Ovidrel®. The patient should be advised of the potential risk of multiple births before starting treatment.

Pulmonary and Vascular Complications

As with other hCG products, a potential for the occurrence of arterial thromboembolism exists.

PRECAUTIONS

General

Careful attention should be given to the diagnosis of infertility in candidates for hCG therapy. (see "Indications and Usage/ Selection of Patients"). After the exclusion of pre-existing conditions, elevations in ALT were found in 10 (3%) of 335 patients receiving Ovidrel® 250 µg, 9 (10%) of 89 patients receiving Ovidrel® 500 µg and in 16 (4.8%) of 328 patients receiving urinary-derived hCG. The elevations ranged up to 1.2 times the upper limit of normal. The clinical significance of these findings is not known.

Information for Patients

Prior to therapy with hCG, patients should be informed of the duration of treatment and monitoring of their condition that will be required. The risks of ovarian hyperstimulation syndrome and multiple births in women (see WARNINGS) and other possible adverse reactions (see "Adverse Reactions") should also be discussed.

Laboratory Tests

In most instances, treatment of women with FSH results only in follicular recruitment and development. In the absence of an endogenous LH surge, hCG is given when monitoring of the patient indicates that sufficient follicular development has occurred. This may be estimated by ultrasound alone or in combination with measurement of serum estradiol levels. The combination of both ultrasound and serum estradiol measurement are useful for monitoring the development of follicles, for timing of the ovulatory trigger, as well as for detecting ovarian enlargement and minimizing the risk of the Ovarian Hyperstimulation Syndrome and multiple gestation. It is recommended that the number of growing follicles be confirmed using ultrasonography because serum estrogens do not give an indication of the size or number of follicles.

Human chorionic gonadotropins can crossreact in the radioimmunoassay of gonadotropins, especially luteinizing hormone. Each individual laboratory should establish the degree of crossreactivity with their gonadotropin assay. Physicians should make the laboratory aware of patients on hCG if gonadotropin levels are requested.

The clinical confirmation of ovulation, with the exception of pregnancy, is obtained by direct and indirect indices of progesterone production. The indices most generally used are as follows:

1. A rise in basal body temperature
2. Increase in serum progesterone and
3. Menstruation following a shift in basal body temperature

When used in conjunction with the indices of progesterone production, sonographic visualization of the ovaries will assist in determining if ovulation has occurred. Sonographic evidence of ovulation may include the following:

1. Fluid in the cul-de-sac
2. Ovarian stigmata
3. Collapsed follicle
4. Secretory endometrium

Accurate interpretation of the indices of ovulation require a physician who is experienced in the interpretation of these tests.

Carcinogenesis, Mutagenesis, Impairment of Fertility

Long-term studies to evaluate the carcinogenic potential of Ovidrel® in animals have not been performed. In vitro genotoxicity testing of Ovidrel® in bacteria and mammalian cell lines, chromosome aberration assay in human lymphocytes and in-vivo mouse micronucleus have shown no indication of genetic defects.

Pregnancy

Intrauterine death and impaired parturition were observed in pregnant rats given a dose of urinary-hCG (500 IU) equivalent to three times the maximum human dose of 10,000 USP, based on body surface area.

Nursing Mothers

It is not known whether this drug is excreted in human milk. Because many drugs are excreted in human milk, caution should be exercised if hCG is administered to a nursing woman.

Pediatric Patients

Safety and effectiveness in pediatric patients has not been established.

Geriatric Patients

Safety and effectiveness in geriatric patients has not been established.

ADVERSE REACTIONS

(see WARNINGS)

The safety of Ovidrel® was examined in four clinical studies that treated 752 patients of whom 335 received Ovidrel® 250 µg following follicular recruitment with gonadotropins. When patients enrolled in four clinical studies (3 in ART and one in OI) were injected subcutaneously with either Ovidrel® or an approved urinary-derived hCG, 14.6 % (49 of 335 patients) in the Ovidrel® 250 µg group experienced application site disorders compared to 28% (92 of 328 patients) in the approved u-hCG group. Adverse events reported for Ovidrel® 250 µg occurring in at least 2% of patients (regardless of causality) are listed in Table 9 for the 3 ART studies and in Table 10 for the single OI study.

Table 9: Incidence of Adverse Events of r-hCG in ART (Studies 7648, 7927, 9073)
Body System | Ovidrel® 250 µg (n=236)
Preferred Term | Incidence Rate % (n)
At Least One Adverse Event | 33.1% (78)
Application Site Disorders | 14.0% (33)
Injection Site Pain | 7.6% (18)
Injection Site Bruising | 4.7% (11)
Gastro-Intestinal System Disorders | 8.5% (20)
Abdominal Pain | 4.2% (10)
Nausea | 3.4% (8)
Vomiting | 2.5% (6)
Secondary Terms (Post-Operative Pain) | 4.7% (11)
Post-Operative Pain | 4.7% (11)

Adverse events not listed in Table 9 that occurred in less than 2% of patients treated with Ovidrel® 250 µg whether or not considered causally related to Ovidrel®, included: injection site inflammation and reaction, flatulence, diarrhea, hiccup, ectopic pregnancy, breast pain, intermenstrual bleeding, vaginal hemorrhage, cervical lesion, leukorrhea, ovarian hyperstimulation, uterine disorders, vaginitis, vaginal discomfort, body pain, back pain, fever, dizziness, headache, hot flashes, malaise, paraesthesias, rash, emotional lability, insomnia, upper respiratory tract infection, cough, dysuria, urinary tract infection, urinary incontinence, albuminuria, cardiac arrhythmia, genital moniliasis, genital herpes, leukocytosis, heart murmur and cervical carcinoma.

Table 10: Incidence of Adverse Events of r-hCG in Ovulation Induction (Study 8209)
Body System | Ovidrel® 250 µg (n=99)
Preferred Term | Incidence Rate % (n)
At Least One Adverse Event | 26.2% (26)
Application Site Disorders | 16.2% (16)
Injection site pain | 8.1% (8)
Injection site inflammation | 2.0% (2)
Injection site bruising | 3.0% (3)
Injection site reaction | 3.0% (3)
Reproductive Disorders, Female | 7.1% (7)
Ovarian cyst | 3.0% (3)
Ovarian hyperstimulation | 3.0% (3)
Gastro-Intestinal System Disorders | 4.0% (4)
Abdominal pain | 3.0% (3)

Additional adverse events not listed in Table 10 that occurred in less than 2% of patients treated with Ovidrel® 250 µg, whether or not considered causally related to Ovidrel®, included: breast pain, flatulence, abdominal enlargement, pharyngitis, upper respiratory tract infection, hyperglycemia and pruritis.

The following medical events have been reported subsequent to pregnancies resulting from hCG therapy in controlled clinical studies:

1. Spontaneous Abortion
2. Ectopic Pregnancy
3. Premature Labor
4. Postpartum Fever
5. Congenital Abnormalities

Of 125 clinical pregnancies reported following treatment with FSH and Ovidrel® 250 µg or 500 µg, three were associated with a congenital anomaly of the fetus or newborn. Among patients receiving Ovidrel® 250 µg, cranial malformation was detected in the fetus of one woman and a chromosomal abnormality (47, XXX) in another. These events were judged by the investigators to be of unlikely or unknown relation to treatment. These three events represent an incidence of major congenital malformations of 2.4%, which is consistent with the reported rate for pregnancies resulting from natural or assisted conception. In a woman who received Ovidrel® 500 µg, one birth in a set of triplets was associated with Down's syndrome and atrial septal defect. This event was considered to be unrelated to the study drug.

The following adverse reactions have been previously reported during menotropin therapy:

1. Pulmonary and vascular complications (see "Warnings")
2. Adnexal torsion (as a complication of ovarian enlargement)
3. Mild to moderate ovarian enlargement
4. Hemoperitoneum

There have been infrequent reports of ovarian neoplasms, both benign and malignant, in women who have undergone multiple drug regimens for ovulation induction; however, a causal relationship has not been established.

Post-Marketing Experience

In addition to adverse events reported from clinical trials, the following events have been reported during post-marketing use of Ovidrel®. Therefore, these events were reported from a population of uncertain size, the frequency or causal relationship to Ovidrel® cannot be reliably determined.

- Cases of allergic reactions, including anaphylactic reactions and mild reversible skin rashes have been reported in patients treated with Ovidrel® since market introduction. The causal relationship is unknown.
- Thromboembolic events both in association with, and separate from, the Ovarian Hyperstimulation Syndrome (see "WARNINGS")

DOSAGE AND ADMINISTRATION

For Subcutaneous Use Only

Infertile Women Undergoing Assisted Reproductive Technologies (ART)

Ovidrel® PreFilled Syringe 250 µg should be administered one day following the last dose of the follicle stimulating agent. Ovidrel® PreFilled Syringe should not be administered until adequate follicular development is indicated by serum estradiol and vaginal ultrasonography. Administration should be withheld in situations where there is an excessive ovarian response, as evidenced by clinically significant ovarian enlargement or excessive estradiol production.

Infertile Women Undergoing Ovulation Induction (OI)

Ovidrel® PreFilled Syringe should not be administered until adequate follicular development is indicated by serum estradiol and vaginal ultrasonography.

Ovidrel® PreFilled Syringe 250 µg should be administered one day following the last dose of the follicle stimulating agent.

Ovidrel® PreFilled Syringe administration should be withheld in situations where there is an excessive ovarian response, as evidenced by multiple follicular development, clinically significant ovarian enlargement or excessive estradiol production.

Directions for Administration of Ovidrel® Prefilled Syringe

Ovidrel® PreFilled Syringe is intended for a single subcutaneous injection. Any unused material should be discarded.

Ovidrel® PreFilled Syringe may be self-administered by the patient. Follow the directions below for injecting Ovidrel® PreFilled Syringe.

Step 1: Wash your hands thoroughly with soap and water.

Step 2: Carefully clean the injection site.

Make yourself comfortable by sitting or lying down. Carefully clean the injection site on the stomach with an alcohol wipe and allow it to air-dry.

Step 3: Administer your injection.

Carefully remove the needle cap from the syringe. Do not touch the needle or allow the needle to touch any surface. Inject the prescribed dose as directed by your doctor, nurse or pharmacist.

Step 4: Gently withdraw the needle.

Discard the needle and syringe into your safety container. Place gauze over the injection site. If any bleeding occurs, apply gentle pressure. If bleeding does not stop within a few minutes, place a clean piece of gauze over the injection site and cover it with an adhesive bandage.

Step 5: Storage and clean up.

Remember that your injection materials must be kept sterile and cannot be reused.

HOW SUPPLIED

Ovidrel® PreFilled Syringe (choriogonadotropin alfa injection) is supplied in a sterile, liquid single dose pre-filled 1 mL syringe. Each Ovidrel® PreFilled Syringe is filled with 0.515 mL containing 257.5 µg of choriogonadotropin alfa, 28.1 mg mannitol, 505 µg 85% O-phosphoric acid, 103 µg L-methionine, 51.5 µg Poloxamer 188, Sodium Hydroxide (for pH adjustment), and Water for Injection to deliver 250 µg of choriogonadotropin alfa in 0.5 mL.

The following package combination is available:

- 1 pre-filled syringe containing 250 μg Ovidrel® PreFilled Syringe NDC 44087-1150-1

Storage

The Ovidrel® PreFilled Syringe must be stored refrigerated between 2-8°C (36-46°F) before being dispensed to the patient. Patients should store the pre-filled syringe refrigerated to allow the product to be used until the expiry date shown on the syringe or carton. The Ovidrel® PreFilled Syringe may be stored by the patient for no more than 30 days at room temperature (up to 25°C (77°F) but must be used within those 30 days.

Protect from light.

Store in original package. Discard unused material.

Rx Only

Manufactured For:
EMD Serono, Inc. Rockland, MA 02370

June 2018

PRINCIPAL DISPLAY PANEL - 250 µg/0.5 mL Syringe Carton

OVIDREL®
PreFilled
Syringe
250 µg/0.5 mL
choriogonadotropin alfa injection

NDC 44087-1150-1

For subcutaneous injection
Rx Only

1 Ovidrel® PreFilled Syringe

EMD
SERONO